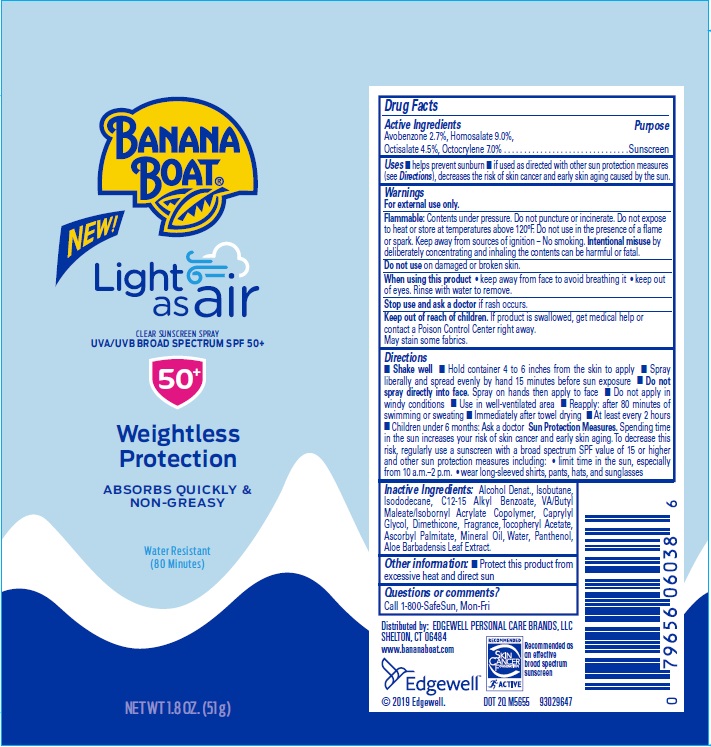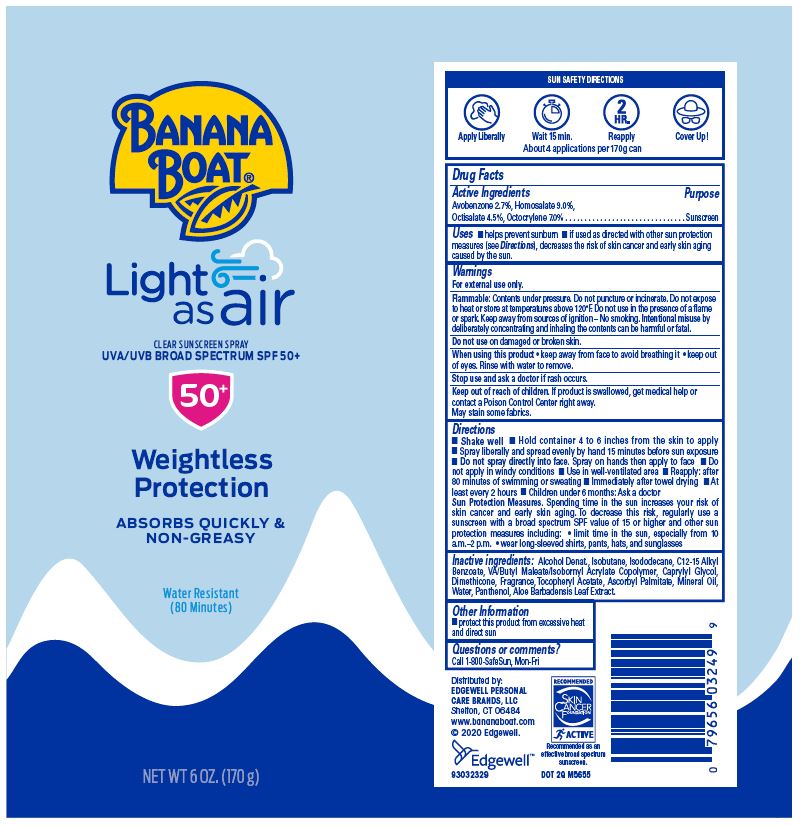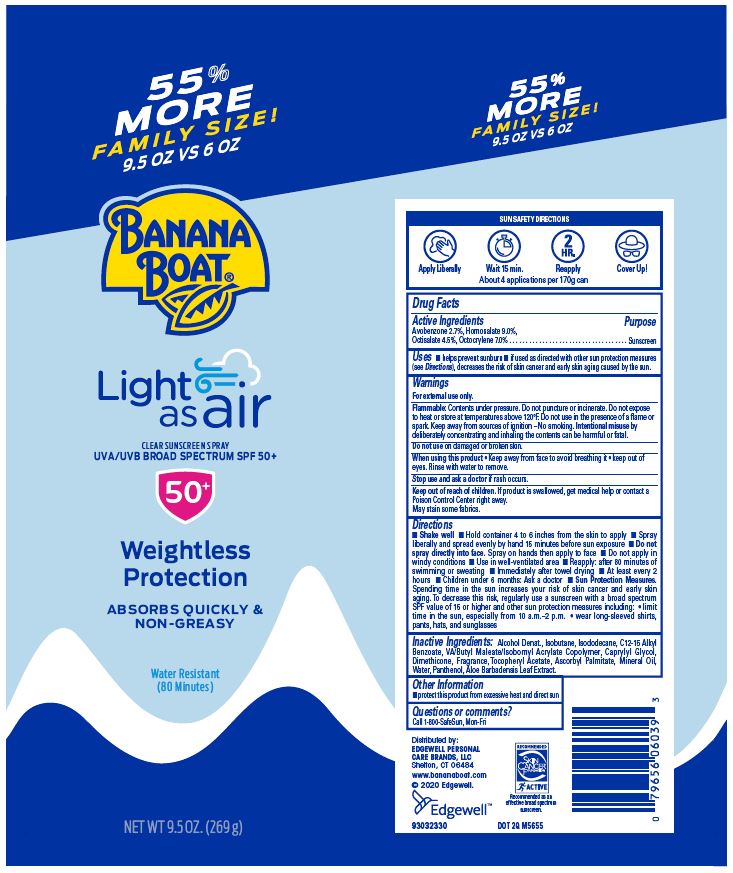 DRUG LABEL: Banana Boat
NDC: 63354-483 | Form: SPRAY
Manufacturer: Edgewell Personal Care Brands LLC
Category: otc | Type: HUMAN OTC DRUG LABEL
Date: 20241027

ACTIVE INGREDIENTS: OCTISALATE 4.5 g/100 g; HOMOSALATE 9 g/100 g; OCTOCRYLENE 7 g/100 g; AVOBENZONE 2.7 g/100 g
INACTIVE INGREDIENTS: .ALPHA.-TOCOPHEROL ACETATE; ALCOHOL; ALKYL (C12-15) BENZOATE; DIMETHICONE; ASCORBYL PALMITATE; PANTHENOL; CAPRYLYL GLYCOL; MINERAL OIL; ISOBUTANE; ISODODECANE; ALOE VERA LEAF; WATER

Active Ingredient

Avobenzone 2.7%, Homosalate 9.0%, Octisalate 4.5%, Octocrylene 7.0%

Purpose

Sunscreen

Uses

Helps prevent sunburn. If used as directed with other sun protection measures (see Directions), decreases the risk of skin cancer and early skin aging caused by the sun.

Warnings

For external use only

May stain some fabrics.

Flammable

Contents under pressure. Do not puncture or incinerate. Do not expose to heat or store at temperatures above 120°F. Do not use in the presence of a flame or spark. Keep away from sources of ignition - No smoking. Intentional misuse by deliberately concentrating and inhaling the contents can be harmful or fatal.

Do not use

on damaged or broken skin

When using this product

Keep away from face to avoid breathing it. Keep out of eyes. Rinse with water to remove.

Stop use and ask a doctor

if rash occurs.

Keep out of reach of children

If product is swallowed, get medical help or contact a Poison Control Center right away.

Directions

• Shake well • Hold container 4 to 6 inches from the skin to apply • Spray liberally and spread evenly by hand 15 minutes before sun exposure • Do not spray directly into face. Spray on hands then apply to face • Do not apply in windy conditions • Use in well-ventilated area • Reapply: after 80 minutes of swimming or sweating • Immediately after towel drying • At least every 2 hours • Children under 6 months: Ask a doctor Sun Protection Measures. Spending time in the sun increases your risk of skin cancer and early skin aging. To decrease this risk, regularly use a sunscreen with a broad spectrum SPF value of 15 or higher and other sun protection measures including: • limit time in the sun, especially from 10 a.m. - 2 p.m. • wear long-sleeved shirts,pants, hats, and sunglasses

Inactive Ingredients

Alcohol Denat., Isobutane, Isododecane, C12-15 Alkyl Benzoate, VA/Butyl Maleate/Isobornyl Acrylate Copolymer, Caprylyl Glycol, Dimethicone, Fragrance, Tocopheryl Acetate, Ascorbyl Palmitate, Mineral Oil, Water, Panthenol, Aloe Barbadensis Leaf Extract

Other Information

Protect this product from excessive heat and direct sun.

Questions or Comments?

Call 1-800-SafeSun, Mon-Fri

Principal Display Panel

55% MORE
FAMILY SIZE!
9.5 OZ VS 6 OZ
BANANA BOAT®
Light as air
CLEAR SUNSCREEN SPRAY
UVA/UVB BROAD SPECTRUM SPF 50+
50+
Weightless
Protection
ABSORBS QUICKLY &
NON-GREASY
Water Resistant
(80 Minutes)
NET WT 9.5 OZ. (269 g)

BANANA BOAT®
Light as air
CLEAR SUNSCREEN SPRAY
UVA/UVB BROAD SPECTRUM SPF 50+
50+
Weightless
Protection
ABSORBS QUICKLY &
NON-GREASY
Water Resistant
(80 Minutes)
NET WT 6 OZ. (170 g)

BANANA BOAT®
NEW!
Light as air
CLEAR SUNSCREEN SPRAY
UVA/UVB BROAD SPECTRUM SPF 50+
50+
Weightless Protection
ABSORBS QUICKLY & NON-GREASY
Water Resistant
(80 Minutes)
NET WT 1.8 OZ. (51g)